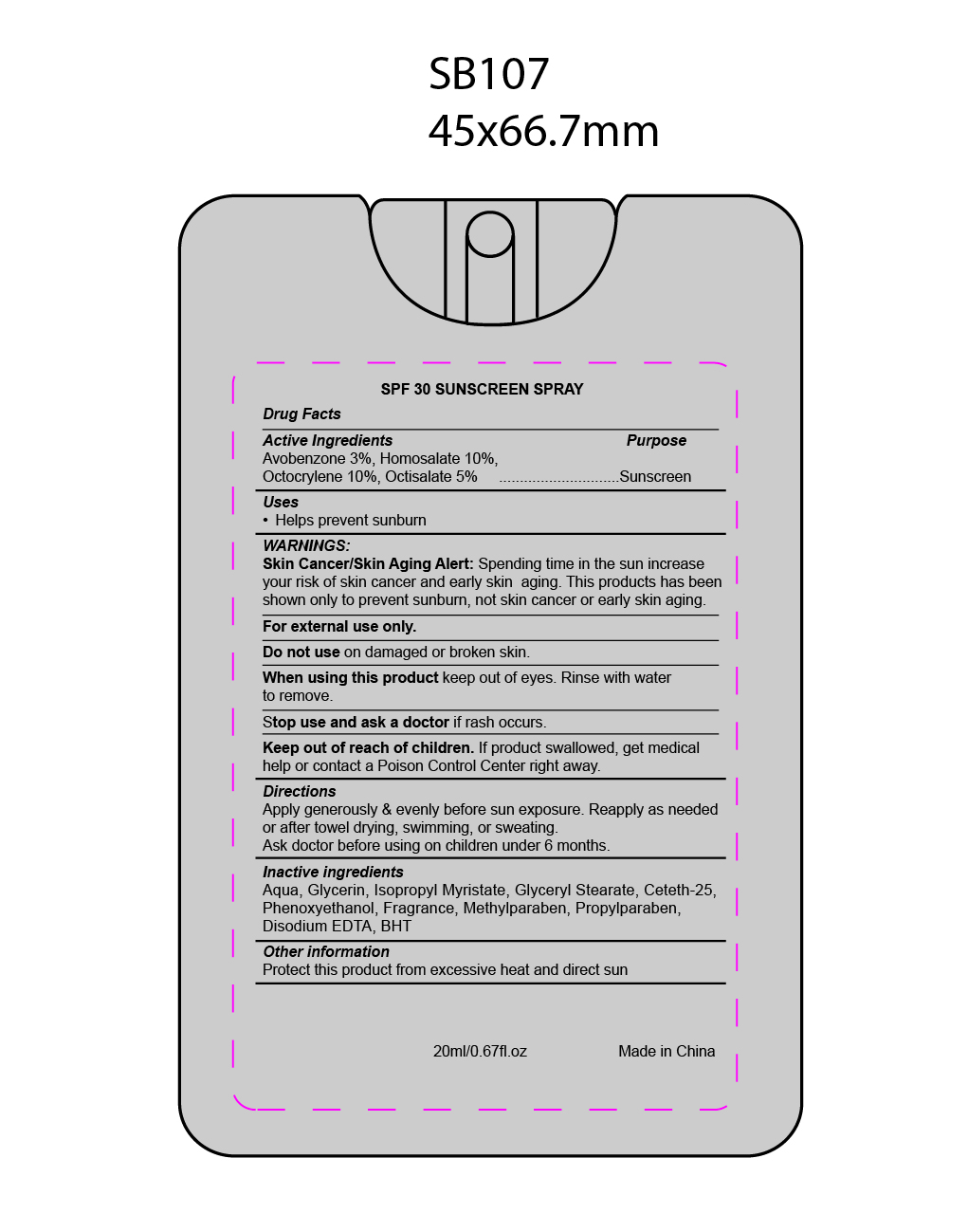 DRUG LABEL: sunscreen
NDC: 82953-003 | Form: SPRAY
Manufacturer: Cosmuses Cosmetics (Ningbo) Co., Ltd.
Category: otc | Type: HUMAN OTC DRUG LABEL
Date: 20241204

ACTIVE INGREDIENTS: HOMOSALATE 10 g/100 mL; OCTOCRYLENE 10 g/100 mL; OCTISALATE 5 g/100 mL; AVOBENZONE 3 g/100 mL
INACTIVE INGREDIENTS: GLYCERIN; ISOPROPYL MYRISTATE; WATER; EDETATE DISODIUM ANHYDROUS; BUTYLATED HYDROXYTOLUENE; PHENOXYETHANOL; METHYLPARABEN; PROPYLPARABEN; GLYCERYL STEARATE SE

SPF30 Sun screen spray

Active Ingredients

Avobenzone 3%

Homosalate 10%

Octocrylene 10%

octisalate 5%

Purpose

Sunscreen

Uses

- Help prevent sunburn

Warnings

Skin Cancer/ Skin Aging Alert: Spending time in the sun increase your risk of skin cancer and early skin aging. This product has been shown only to prevent sunburn, not skin cancer or early skin aging.

Do not use on damaged or broken skin.

When using this product keep out of eyes. RInse with water to remove.

Stop use and ask a doctor if rash occurs.

Keep out of reach of children. If product swallowed, get medical help or contact a Poison Control Center Right away.

Directions

Apply genrously & evenly before sun exposure. Reapply as needed or after towel drying, swimming or sweating.

Ask doctor before using on children under 6 months.

Inactive ingredients

Aqua, Glycerin, Isopropyl Myristate, Glyceryl Stearate, Ceteth-25, phenoxyethanol, Fragrance, Methylparaben, Propylparaben, Disodium EDTA, BHT

Other information

Protect this product from excessive heat and direct sun.